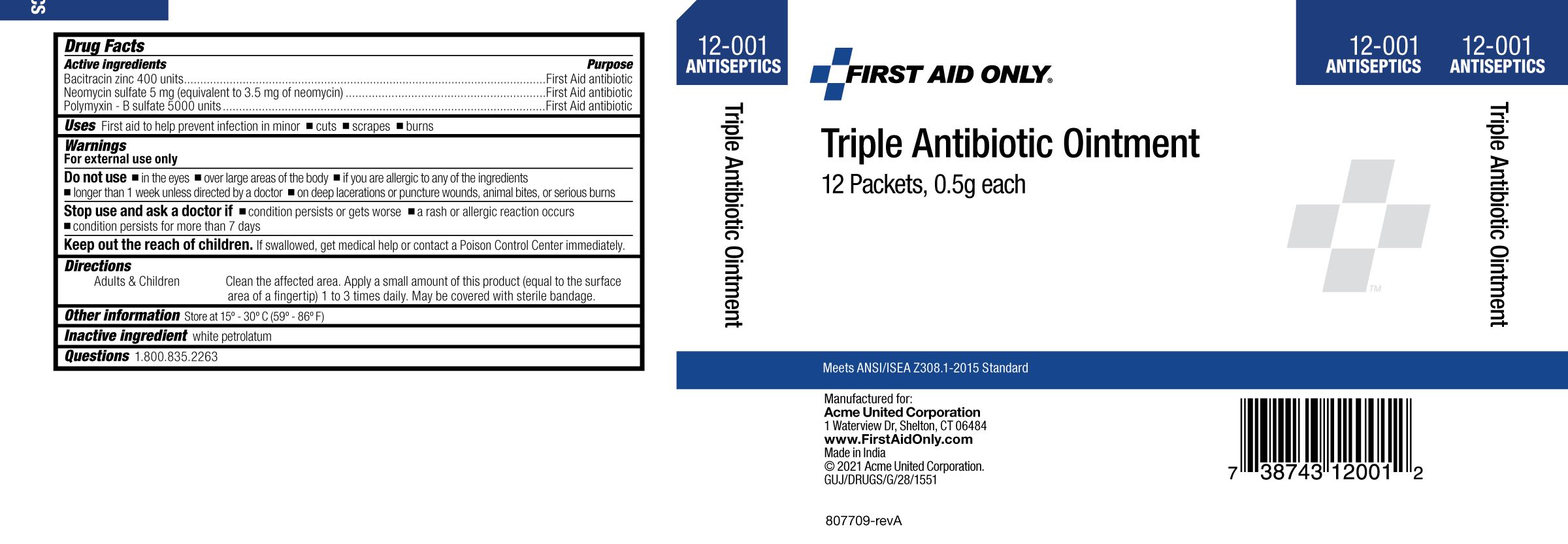 DRUG LABEL: Triple Antibiotic
NDC: 0924-5610 | Form: OINTMENT
Manufacturer: Acme United Corporation
Category: otc | Type: HUMAN OTC DRUG LABEL
Date: 20241119

ACTIVE INGREDIENTS: BACITRACIN ZINC 400 [iU]/1 g; NEOMYCIN SULFATE 5 mg/1 g; POLYMYXIN B SULFATE 5000 [iU]/1 g
INACTIVE INGREDIENTS: PETROLATUM

First Aid Only Triple Antibiotic Ointment

• ACTIVE INGREDIENT

Bacitracin zinc 400 units

Neomycin sulfate 5 mg (equivalent to 3.5 mg. of neomycin base)

Polymyxin - B sulfate 5000 units

Active ingredient (in each gram) | Purpose
Bacitracin Zinc 400 Units | First Aid Antibiotic
Neomycin Sulfate 5mg (Equivalent to 3.5 mg of Neomycin base) | First Aid Antibiotic
Polymyxin B Sulfate 5000 Units | First Aid Antibiotic

• USES

First aid to help prevent infection in minor:

- cuts
- scrapes
- burns

WARNINGS

For external use only

Do not use • in the eyes •over large areas of the body •if you are allergic to any of the ingredients

•longer than 1 week unless directed by a doctor •on deep lacerations or puncture wounds, animal bites, or serious burns

STOP USE AND ASK A DOCTOR IF

•condition persists or gets worse •a rash or allergic reaction occurs

•condition persists for more than 7 days

KEEP OUT OF REACH OF CHILDREN

Keep out the reach of children. If swallowed, get medical help or contact a Poison Control Center immediately.

DIRECTIONS

Adults and Children Clean the affected area. Apply a small amount of product

(equal to the surface area of a fingertip) 1 to 3 times daily. May be covered with a sterile bandage.

OTHER INFORMATION

Store at 15°- 30°C (59°- 86°F)

INACTIVE INGREDIENT

White Petrolatum

Questions 1.800.835.2263

PACKAGE LABEL

Carton Image